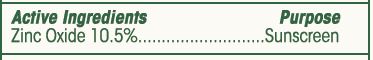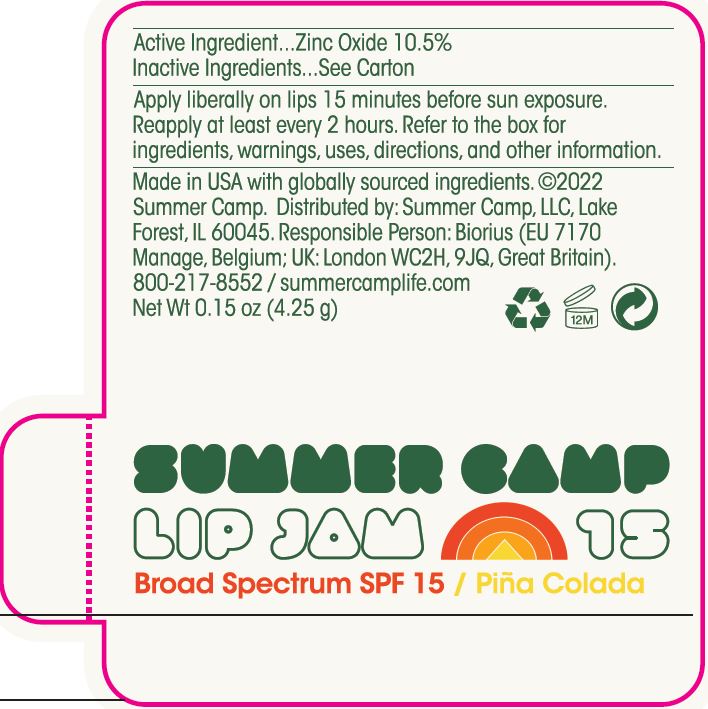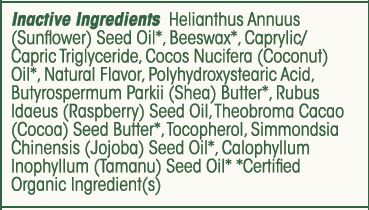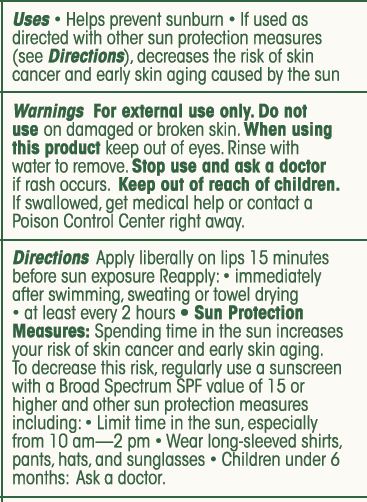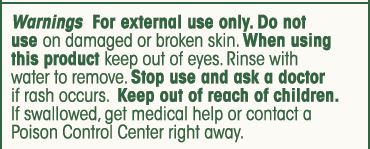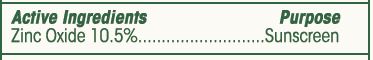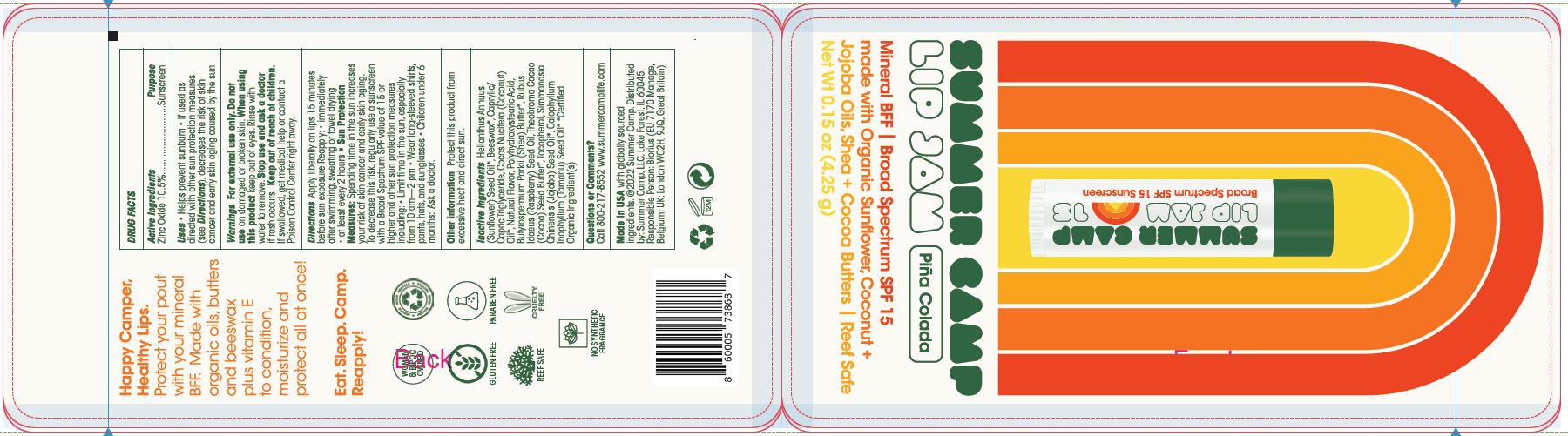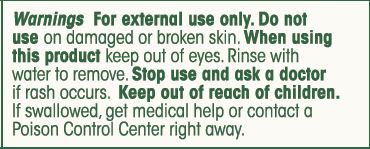 DRUG LABEL: SUNSCREEN
NDC: 62932-267 | Form: STICK
Manufacturer: Private Label Select Ltd CO
Category: otc | Type: HUMAN OTC DRUG LABEL
Date: 20220505

ACTIVE INGREDIENTS: ZINC OXIDE 10.5 g/100 g
INACTIVE INGREDIENTS: MEDIUM-CHAIN TRIGLYCERIDES; SHEA BUTTER; COCOA BUTTER; .ALPHA.-TOCOPHEROL, D-; .GAMMA.-TOCOPHEROL; WHITE WAX; SUNFLOWER OIL; RASPBERRY SEED OIL; .DELTA.-TOCOPHEROL; TAMANU OIL; POLYHYDROXYSTEARIC ACID STEARATE; POLYHYDROXYSTEARIC ACID (2300 MW); JOJOBA OIL; .BETA.-TOCOPHEROL; COCONUT OIL

Soleil Toujours, Summer Camp Mineral BFF Lip Jam, SPF 15